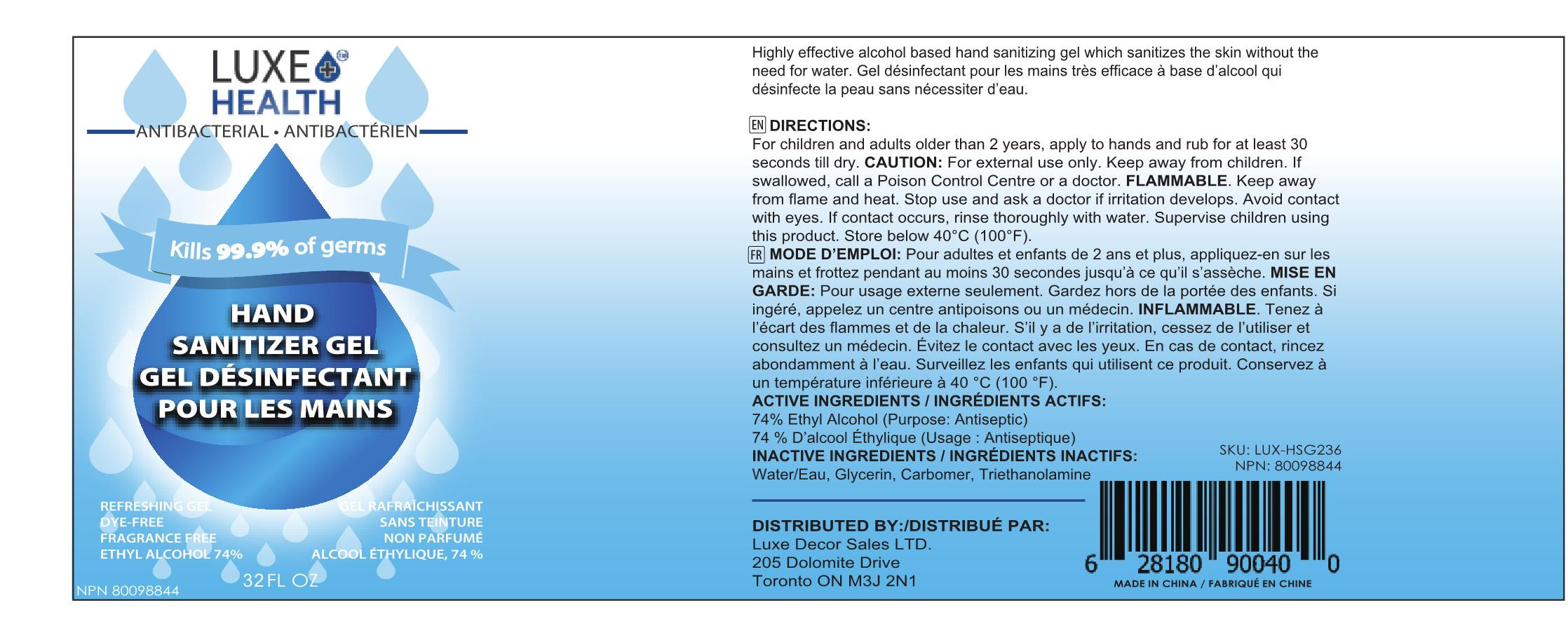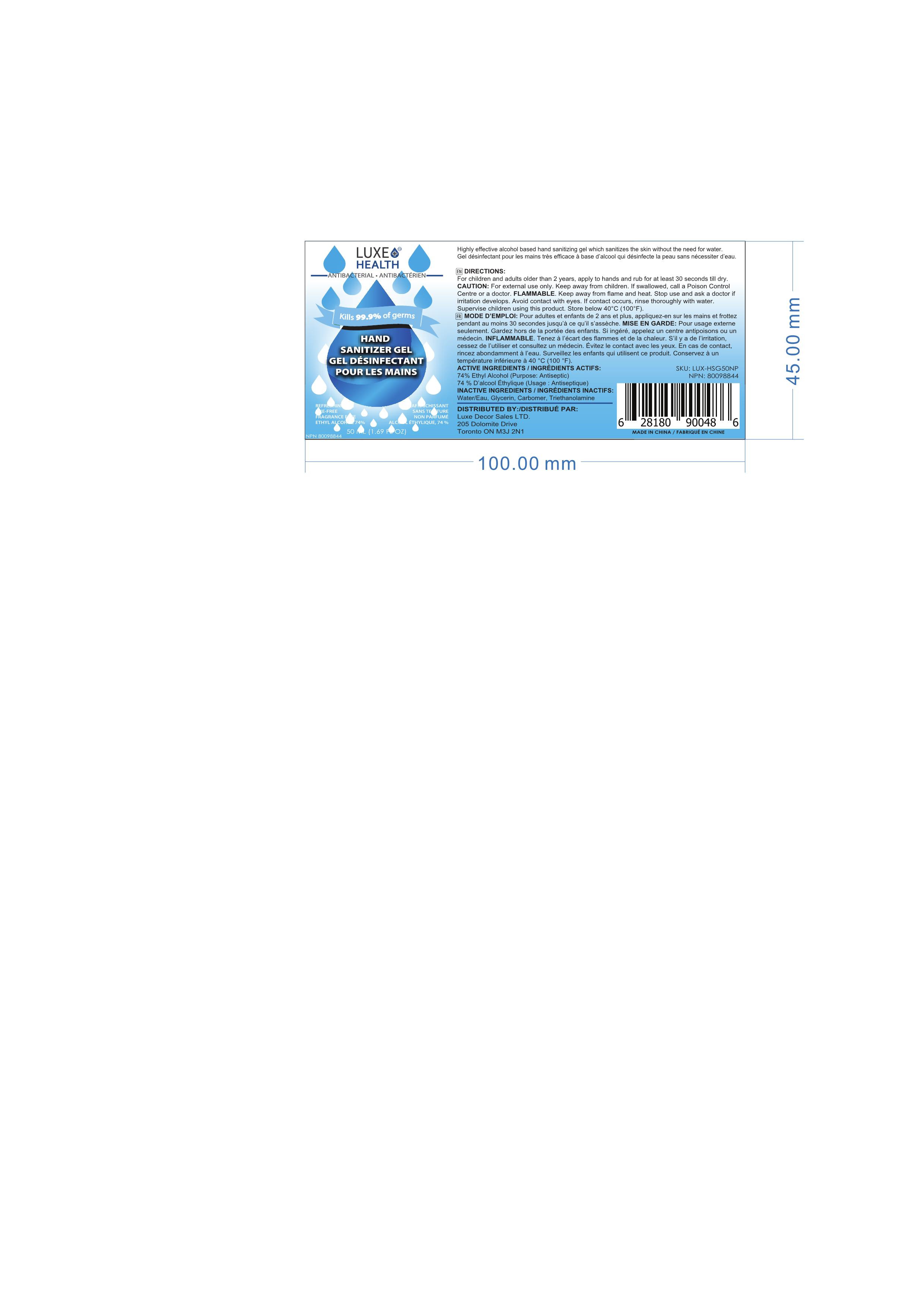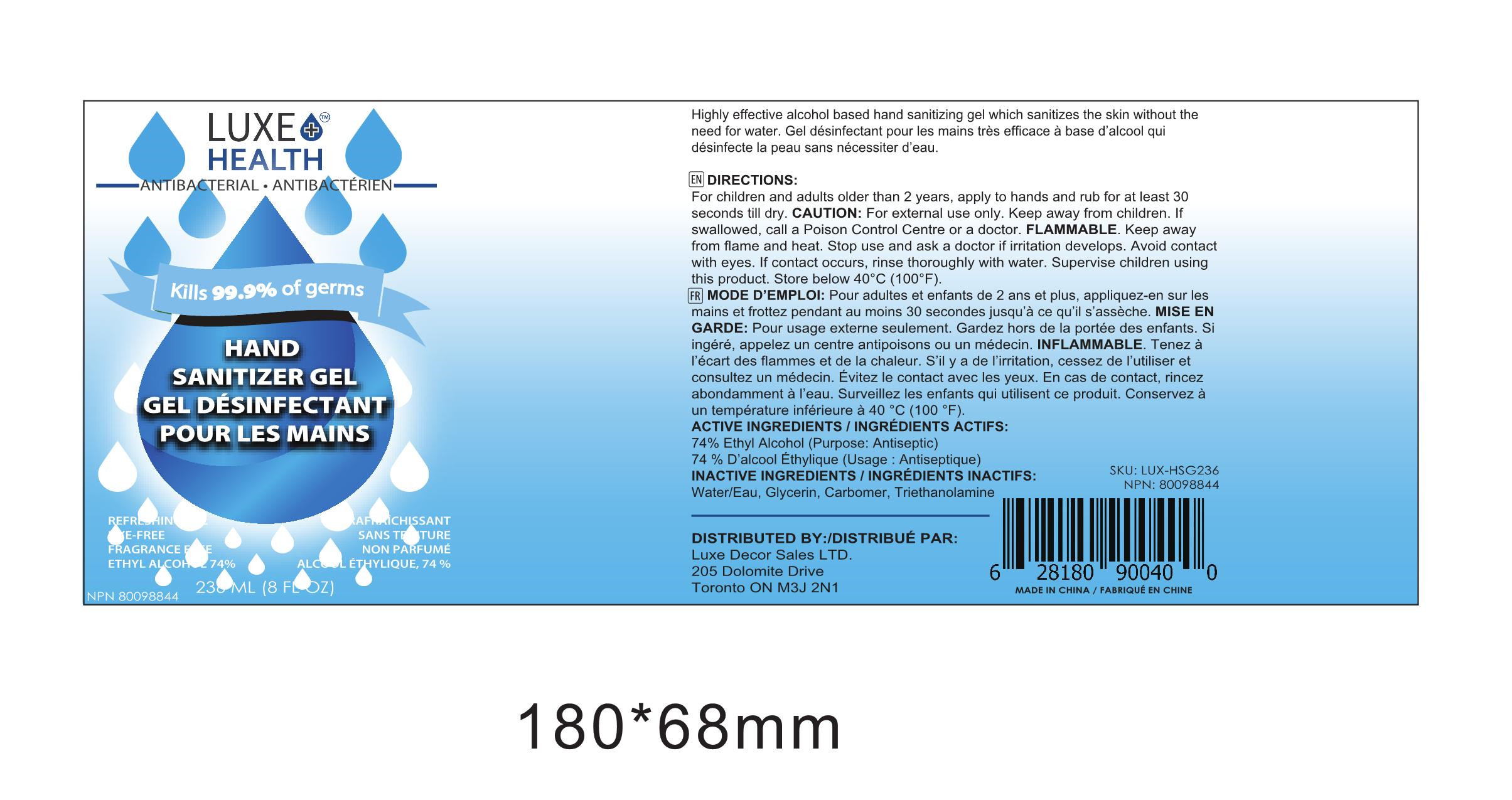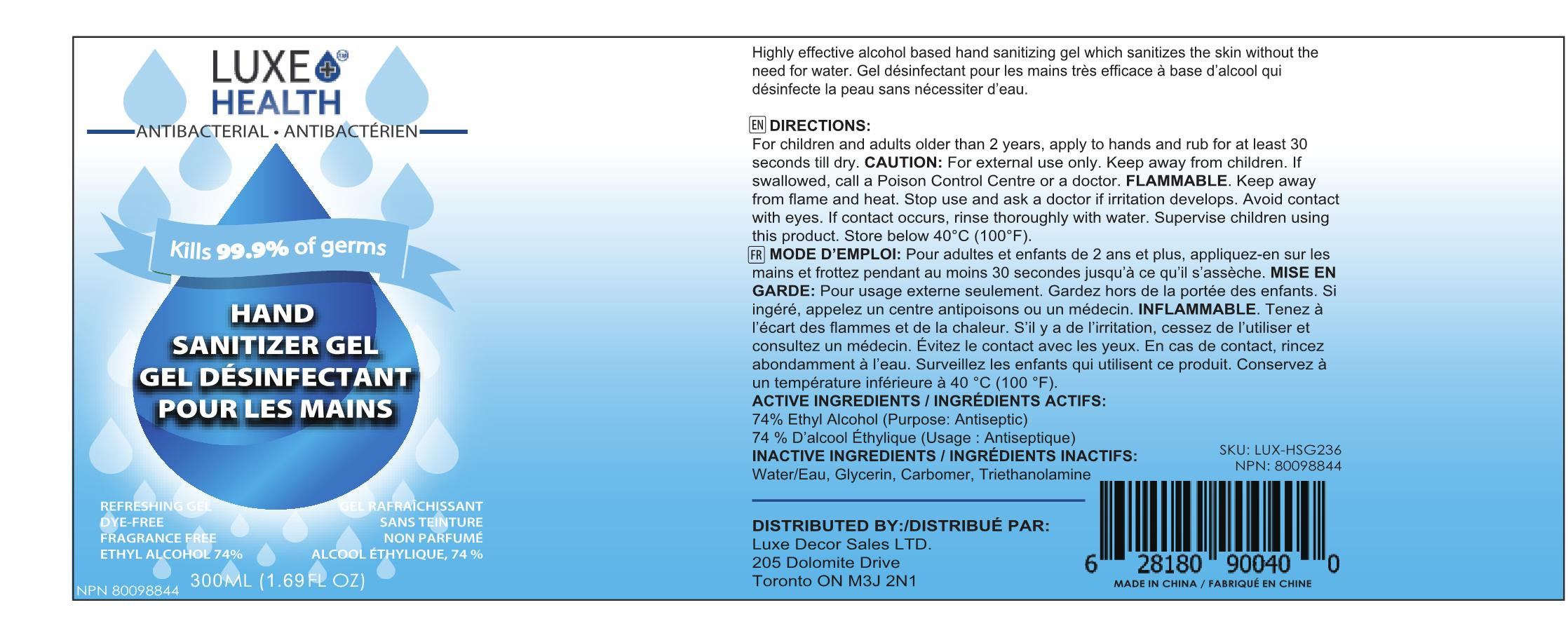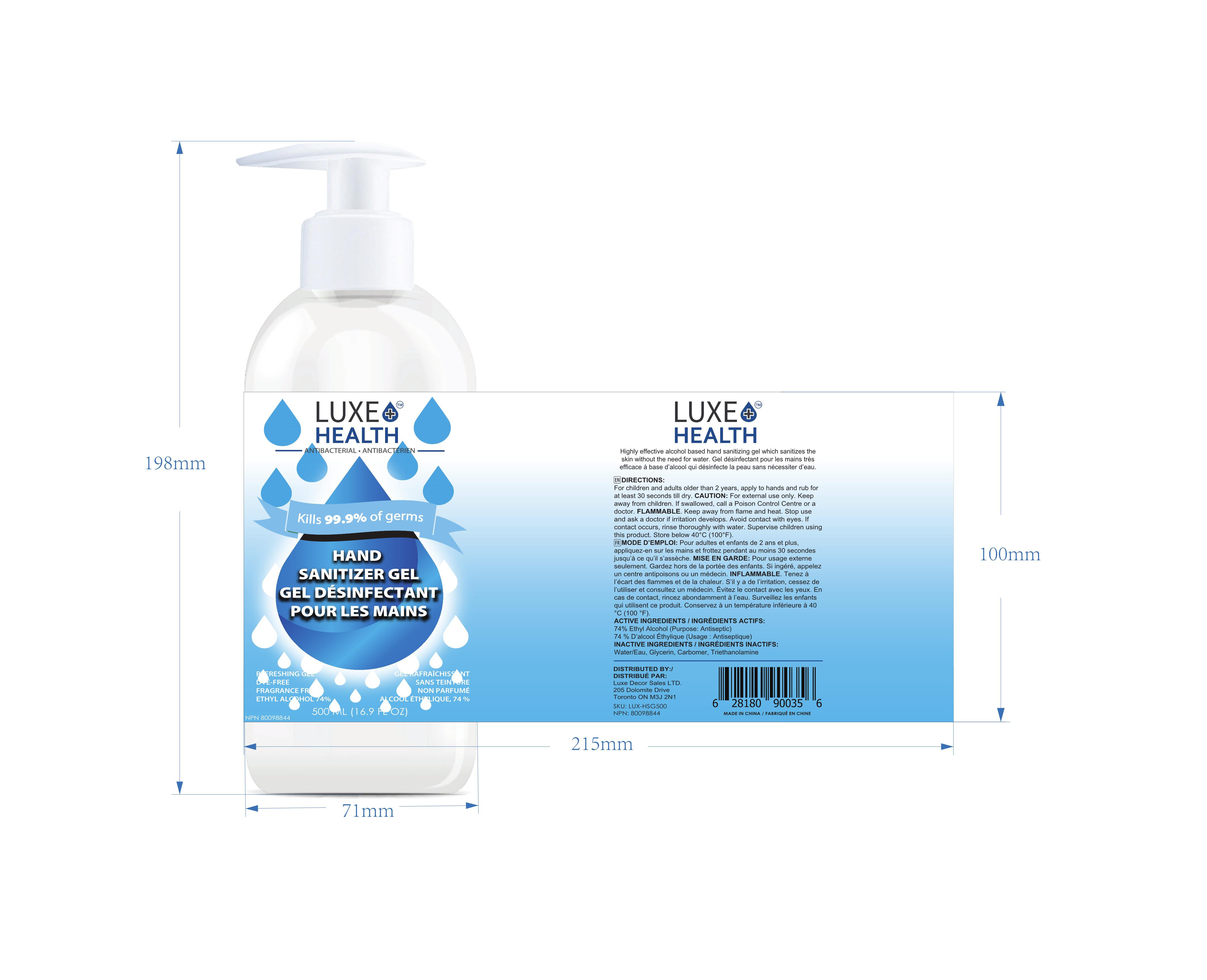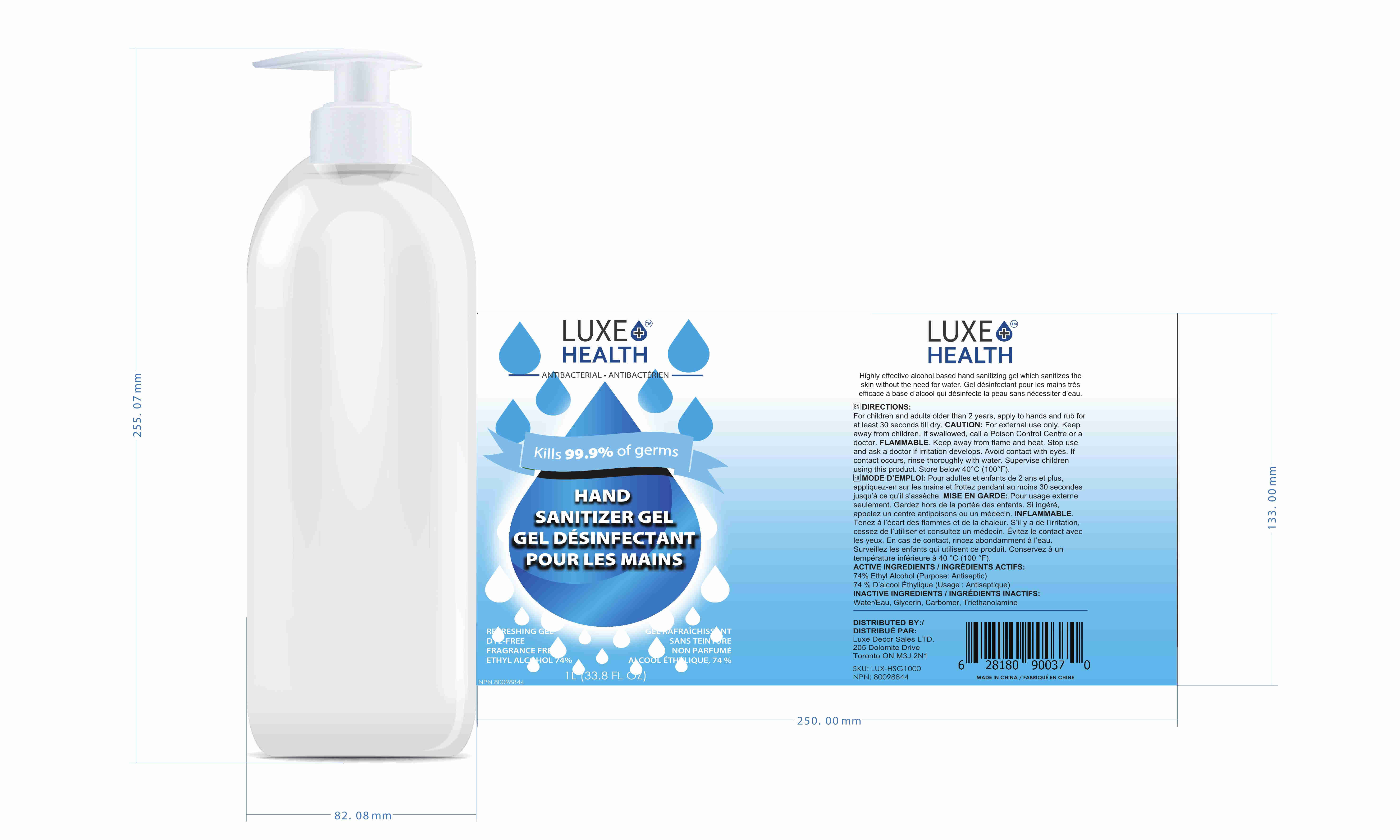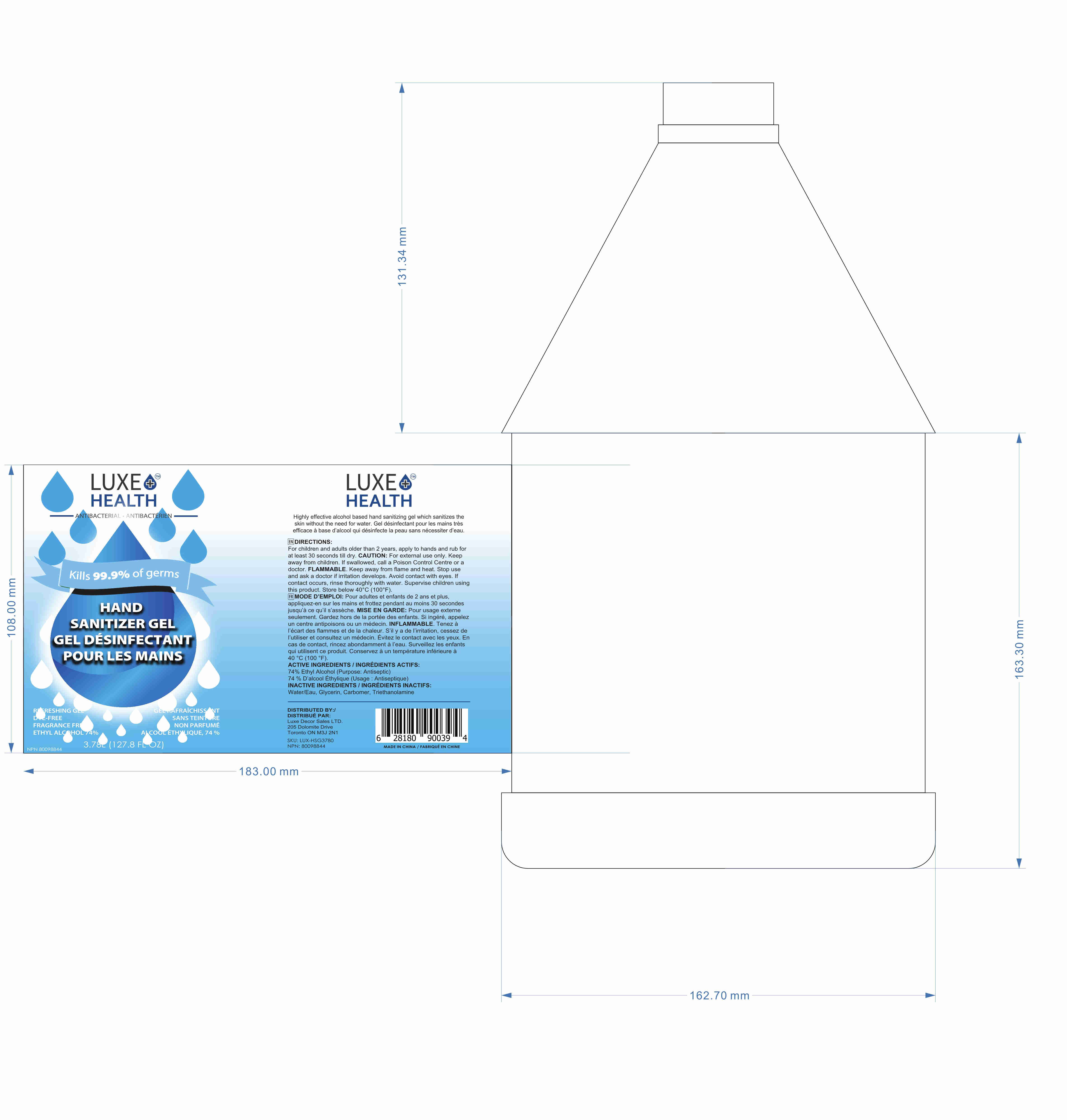 DRUG LABEL: Hand sanitizer gel
NDC: 55467-016 | Form: GEL
Manufacturer: GUANGDONG INTENTLY BIOTECHNOLOGY CO.，LTD.
Category: otc | Type: HUMAN OTC DRUG LABEL
Date: 20201102

ACTIVE INGREDIENTS: ALCOHOL 700 mL/946 mL
INACTIVE INGREDIENTS: TROLAMINE; GLYCERIN; WATER; CARBOMER HOMOPOLYMER, UNSPECIFIED TYPE

DOSAGE AND ADMINISTRATION

Wet hands thoroughly with product and allow to dry without wiping. Supervise children in the use of this product.

STORAGE AND HANDLING

Store below 40°C (100°F).

INACTIVE INGREDIENT

Water

Glycerin

Carbomer

Triethanolamine

INDICATIONS AND USAGE

Highly effective alcohol based hand sanitizing gel which sanitizes the skin without theneed for water.Gel désinfectant pour les mains tres efficace a base d'alcool qui désinfecte la peau sans necessiter d'eau.

ACTIVE INGREDIENT

Alcohol

KEEP OUT OF REACH OF CHILDREN

Keep away from children. lf swallowed, call a Poison Control Centre or a doctor.

PURPOSE

Disinfection
Sterilization
No Rinseing

WARNINGS

For external use only.Keep away from flame and heat. Stop use and ask a doctor if irritation develops.